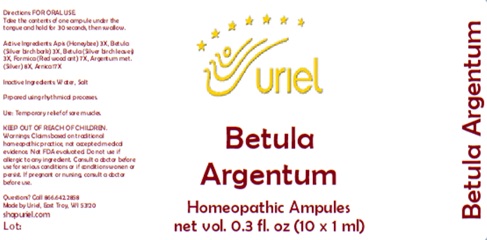 DRUG LABEL: Betula Argentum
NDC: 48951-2063 | Form: LIQUID
Manufacturer: Uriel Pharmacy Inc.
Category: homeopathic | Type: HUMAN OTC DRUG LABEL
Date: 20250627

ACTIVE INGREDIENTS: APIS MELLIFERA 3 [hp_X]/1 mL; BETULA PUBESCENS BARK 3 [hp_X]/1 mL; BETULA PUBESCENS LEAF 3 [hp_X]/1 mL; FORMICA RUFA 7 [hp_X]/1 mL; SILVER 8 [hp_X]/1 mL; ARNICA MONTANA 17 [hp_X]/1 mL
INACTIVE INGREDIENTS: WATER; SODIUM CHLORIDE

Betula Argentum

INDICATIONS AND USAGE

Directions: FOR ORAL USE.

DOSAGE AND ADMINISTRATION

Take the contents of one ampule under the tongue and hold for 30 seconds, then swallow.

ACTIVE INGREDIENT

Active Ingredients: Apis (Honeybee) 3X, Betula (Silver birch bark) 3X, Betula (Silver birch leaves) 3X, Formica (Red wood ant) 7X, Argentum met. (Silver) 8X, Arnica 17X

Inactive Ingredients: Water, Salt

Prepared using rhythmical processes.

PURPOSE

Use: Temporary relief of sore muscles.

KEEP OUT OF REACH OF CHILDREN.

WARNINGS

Warnings: Claims based on traditional homeopathic practice, not accepted medical evidence. Not FDA evaluated. Do not use if allergic to any ingredient. Consult a doctor before use for serious conditions or if conditions worsen or persist. If pregnant or nursing, consult a doctor before use.

Questions? Call 866.642.2858
Made by Uriel, East Troy, WI 53120
shopuriel.com

Lot: